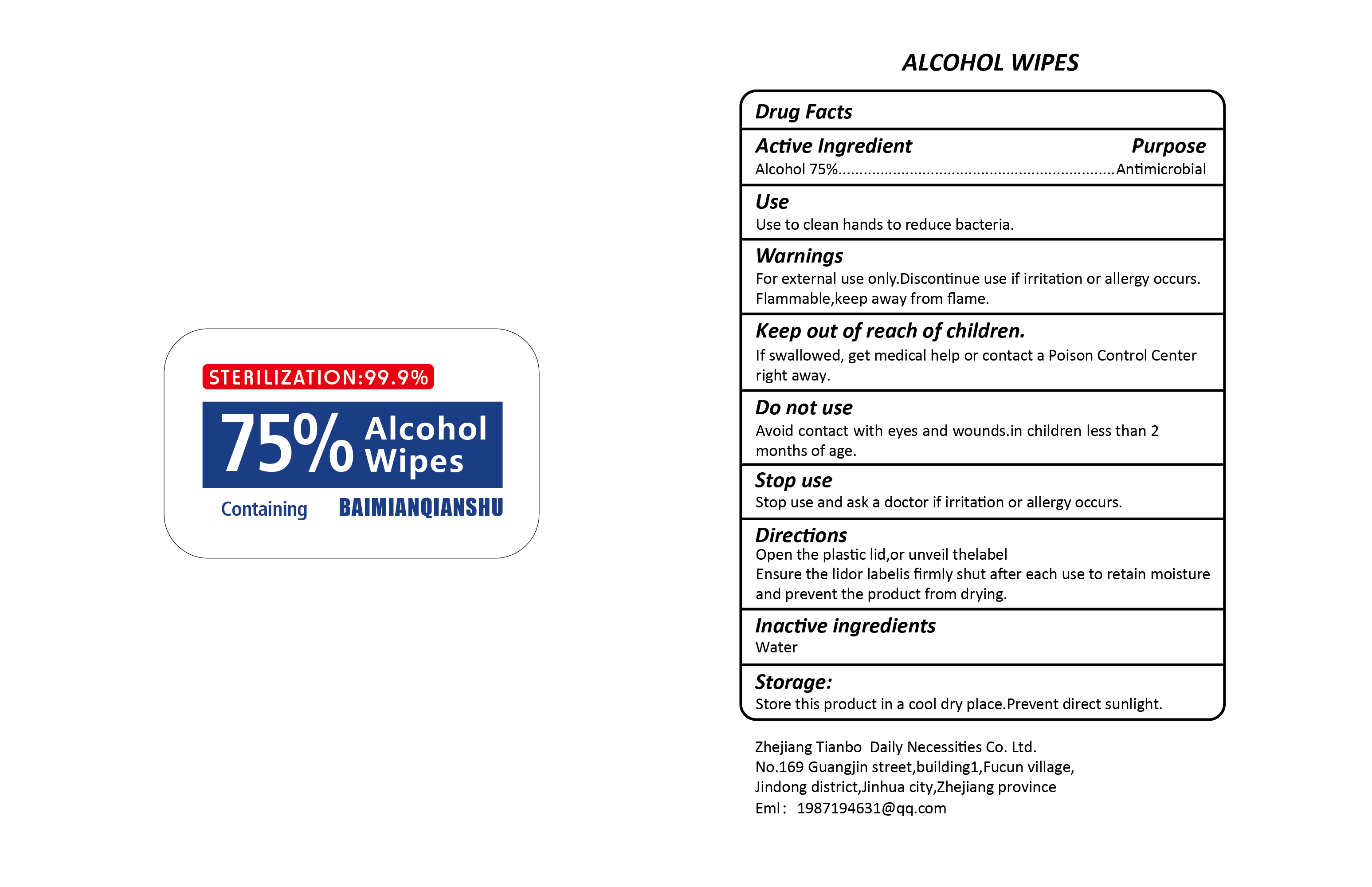 DRUG LABEL: BAIMIANQIANSHU Alcohol Wipes
NDC: 79901-002 | Form: CLOTH
Manufacturer: Zhejiang Tianbo Daily Necessities Co.Ltd
Category: otc | Type: HUMAN OTC DRUG LABEL
Date: 20200811

ACTIVE INGREDIENTS: ALCOHOL 75 mL/100 mL
INACTIVE INGREDIENTS: WATER

Active ingredient

Alcohol 75%

Purpose

Antimicrobial

Use

Use to clean hands to reduce bacteria.

Warnings

For external use only. Discontinue use if irritation or allergy occurs. Flammable, keep away from flame.

Keep out of reach of children

If swallowed, get medical help or contact a Poison Control Center right away.

Do not use

Avoid contact with eyes and wounds. in children less than 2 months of age.

Stop use

Stop use and ask a doctor if irritation or allergy occurs.

Directions

Open the plastic lid, or unveil the label.

Ensure the lidor labelis firmly shut after each use to retain moisture and prevent the product from drying.

Inactive ingredients

Water

Storage

Store this product in a cool dry place. Prevent direct sunlight.